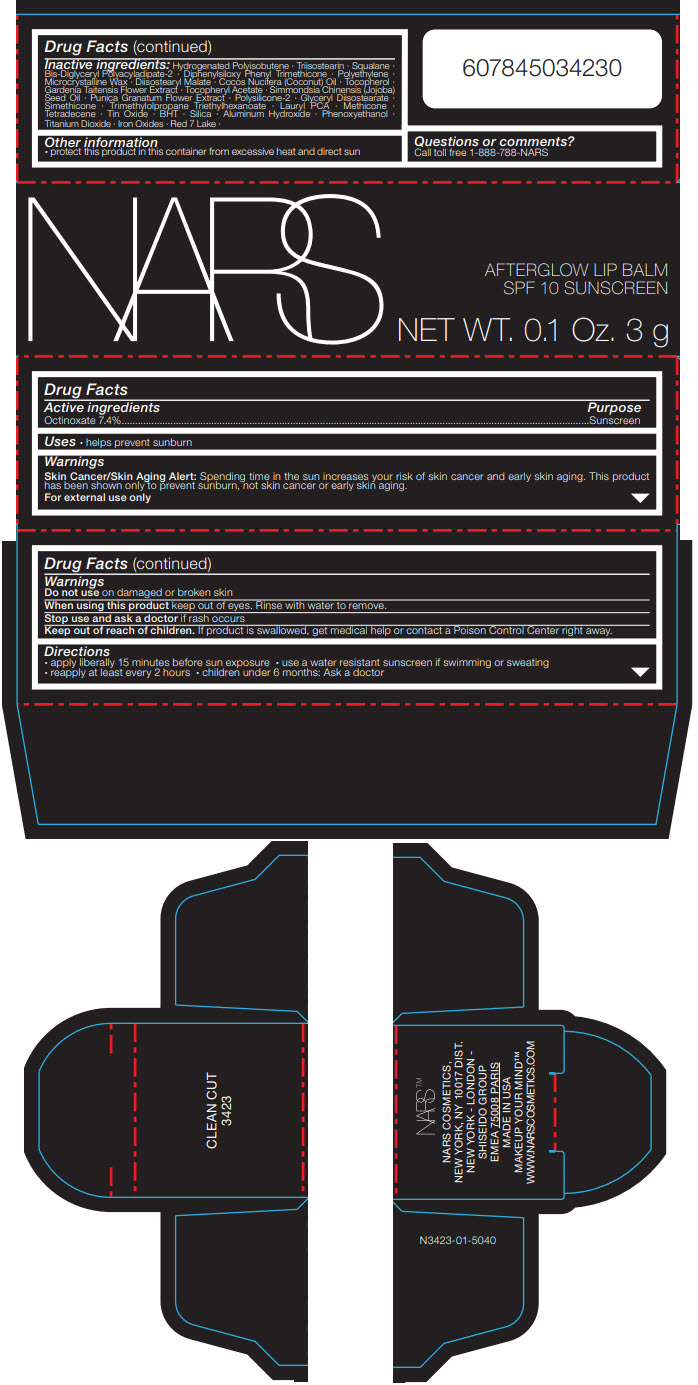 DRUG LABEL: NARS AFTERGLOW LIP BALM CLEAN CUT
NDC: 13734-160 | Form: STICK
Manufacturer: NARS Cosmetics
Category: otc | Type: HUMAN OTC DRUG LABEL
Date: 20190109

ACTIVE INGREDIENTS: OCTINOXATE 222 mg/3 g
INACTIVE INGREDIENTS: HYDROGENATED POLYISOBUTENE (1300 MW); TRIISOSTEARIN; SQUALANE; BIS-DIGLYCERYL POLYACYLADIPATE-2; DIPHENYLSILOXY PHENYL TRIMETHICONE; HIGH DENSITY POLYETHYLENE; MICROCRYSTALLINE WAX; DIISOSTEARYL MALATE; COCONUT OIL; GLYCERYL DIISOSTEARATE; PHENOXYETHANOL; TITANIUM DIOXIDE; GARDENIA TAITENSIS FLOWER; .ALPHA.-TOCOPHEROL ACETATE, DL-; TRIMETHYLOLPROPANE TRIETHYLHEXANOATE; LAURYL PIDOLATE; FERRIC OXIDE RED; FERRIC OXIDE YELLOW; FERROSOFERRIC OXIDE; JOJOBA OIL; BUTYLATED HYDROXYTOLUENE; SILICON DIOXIDE; ALUMINUM HYDROXIDE; .ALPHA.-TOCOPHEROL; METHICONE (20 CST); 1-TETRADECENE; STANNIC OXIDE

NARS AFTERGLOW LIP BALM CLEAN CUT

Drug Facts

Active ingredients

Octinoxate 7.4%

Purpose

Sunscreen

Uses

- helps prevent sunburn

Warnings

Skin Cancer/Skin Aging Alert

Spending time in the sun increases your risk of skin cancer and early skin aging. This product has been shown only to prevent sunburn, not skin cancer or early skin aging.

For external use only

Do not use on damaged or broken skin

When using this product keep out of eyes. Rinse with water to remove.

Stop use and ask a doctor if rash occurs

Keep out of reach of children. If product is swallowed, get medical help or contact a Poison Control Center right away.

Directions

- apply liberally 15 minutes before sun exposure
- use a water resistant sunscreen if swimming or sweating
- reapply at least every 2 hours
- children under 6 months: Ask a doctor

Inactive ingredients

Hydrogenated Polyisobutene ∙ Triisostearin ∙ Squalane ∙ Bis-Diglyceryl Polyacyladipate-2 ∙ Diphenylsiloxy Phenyl Trimethicone ∙ Polyethylene ∙ Microcrystalline Wax ∙ Diisostearyl Malate ∙ Cocos Nucifera (Coconut) Oil ∙ Tocopherol ∙ Gardenia Taitensis Flower Extract ∙ Tocopheryl Acetate ∙ Simmondsia Chinensis (Jojoba) Seed Oil ∙ Punica Granatum Flower Extract ∙ Polysilicone-2 ∙ Glyceryl Diisostearate ∙ Simethicone ∙ Trimethylolpropane Triethylhexanoate ∙ Lauryl PCA ∙ Methicone ∙ Tetradecene ∙ Tin Oxide ∙ BHT ∙ Silica ∙ Aluminum Hydroxide ∙ Phenoxyethanol ∙ Titanium Dioxide ∙ Iron Oxides ∙ Red 7 Lake ∙

Other information

- protect this product in this container from excessive heat and direct sun

Questions or comments?

Call toll free 1-888-788-NARS

PRINCIPAL DISPLAY PANEL - 3 g Cartridge Carton

NARS

AFTERGLOW LIP BALM
SPF 10 SUNSCREEN

NET WT. 0.1 Oz. 3 g